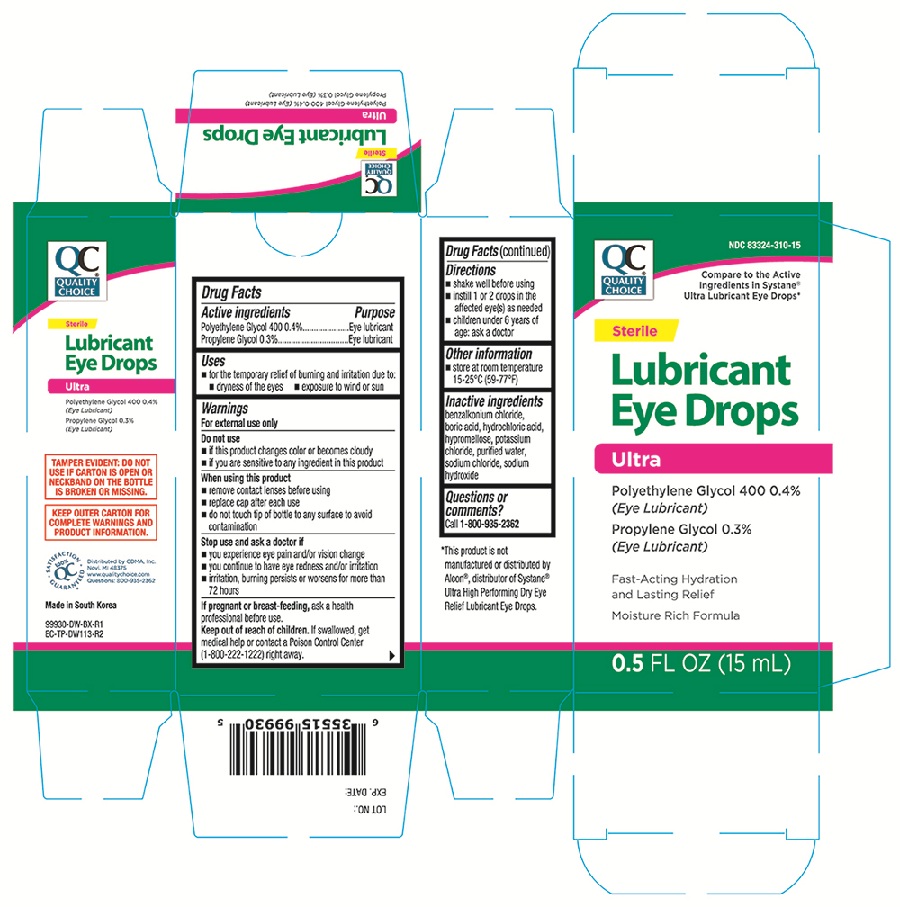 DRUG LABEL: Quality Choice Lubricant
NDC: 83324-310 | Form: SOLUTION/ DROPS
Manufacturer: Chain Drug Marketing Association, Inc.
Category: otc | Type: HUMAN OTC DRUG LABEL
Date: 20251219

ACTIVE INGREDIENTS: PROPYLENE GLYCOL 3 mg/1 mL; POLYETHYLENE GLYCOL 400 4 mg/1 mL
INACTIVE INGREDIENTS: BORIC ACID; BENZALKONIUM CHLORIDE; HYDROCHLORIC ACID; POTASSIUM CHLORIDE; SODIUM CHLORIDE; HYPROMELLOSES; SODIUM HYDROXIDE; WATER

QC Ultra Lubricant 99930 Eye Drops 0.5fl.oz (NBE Systane Ultra)

Active ingredients Purpose

Polyethylene Glycol 400 0.4%...........Eye lubricant

Propylene Glycol 0.3%.......................Eye lubricant

Uses

- for temporary relief of burning and irritation due to:
- dryness of the eyes
- exposure to wind or sun

Warnings

For external use only

Do not use

- if this product changes color or becomes cloudy
- if you are sensitive to any ingredient in this product

When using this product

- remove contact lenses before using
- replace cap after each use
- do not touch tip of bottle to any surface to avoid contamination

Stop use and ask a doctor if

- you experience eye pain and/or vision change
- you continue to have eye redness and/or irritation
- irritation, burning persists or worsens for more than 72 hours

PREGNANCY OR BREAST FEEDING

If pregnant or breast-feeding, ask a health professional before use.

Keep out of reach of children. If swallowed, get medical help or contact or contact a Poison Control Center (1-800-222-1222) right away.

INDICATIONS AND USAGE

- shake well before using
- istill 1 or 2 drops in the affected eye(s) as needed
- children under 6 years of age: ask a doctor

Other information

- store at room temperature 15-25°C (59-77°F)

Inactive ingredients

benzalkonium chloride, boric acid, hydrochloric acid, hypromellose, potassium chloride, purified water, sodium chloride, sodium hydroxide

DOSAGE AND ADMINISTRATION

Distributed by CDMA, Inc.

Novi, MI 48375

Made in South Korea